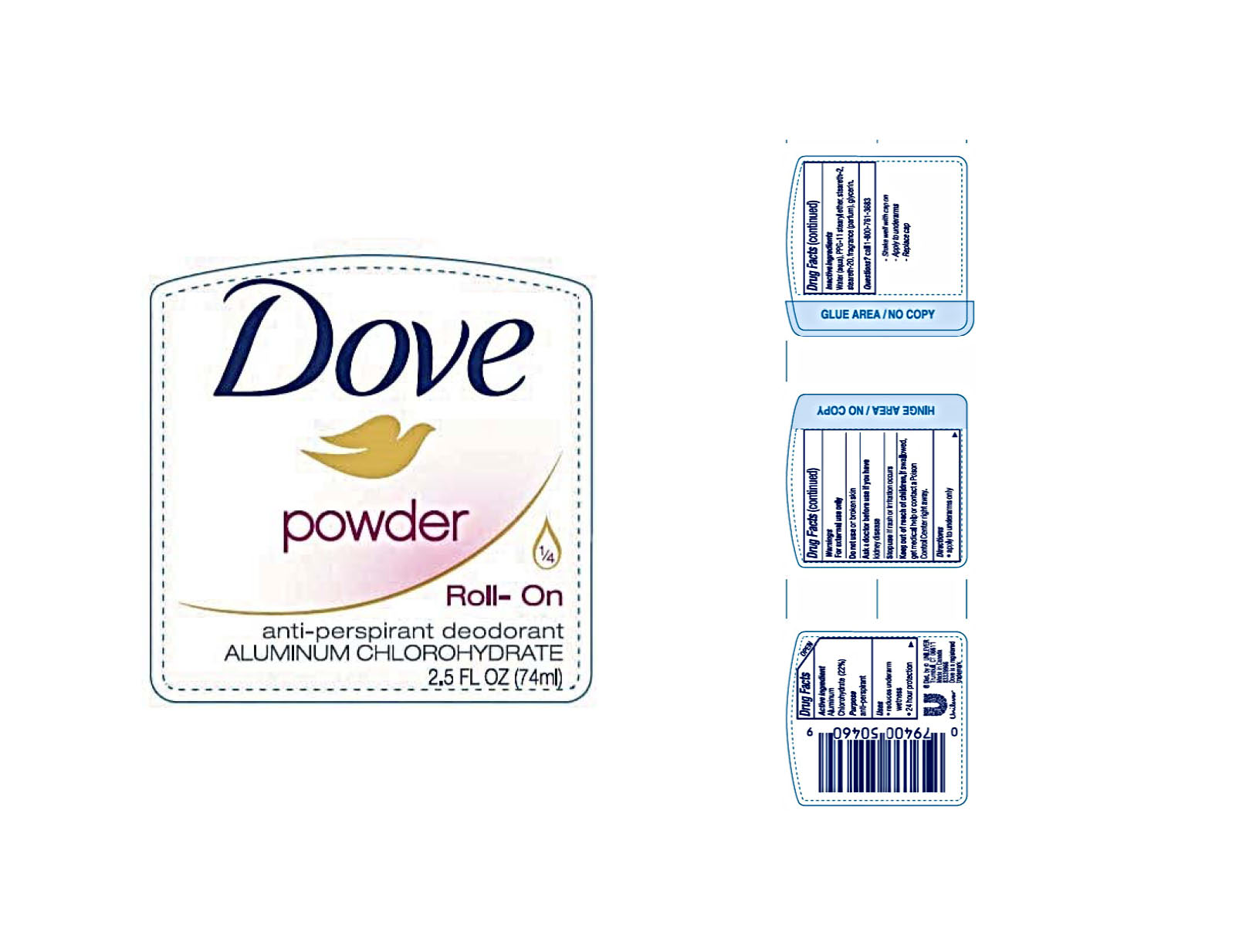 DRUG LABEL: Dove
NDC: 64942-1578 | Form: LIQUID
Manufacturer: Conopco Inc. d/b/a/ Unilever
Category: otc | Type: HUMAN OTC DRUG LABEL
Date: 20241024

ACTIVE INGREDIENTS: ALUMINUM CHLOROHYDRATE 22 g/100 mL
INACTIVE INGREDIENTS: WATER; PPG-11 STEARYL ETHER; STEARETH-20; GLYCERIN; STEARETH-2

Dove Powder Roll-On Antiperspirant Deodorant

DOVE POWDER ROLL-ON ANTIPERSPIRANT DEODORANT - aluminum chlorohydrate liquid

Dove Powder Roll-On AntiPerspirant Deodorant

Drug Facts

Active ingredient

Aluminum Chlorohydrate (22.0%)

Purpose

antiperspirant

Uses

• reduces underarm wetness
• 24 hour protection

Warnings

• For external use only.
• Do not use on broken skin .
• Ask a doctor before use if you have kidney disease.
• Stop use if rash or irritation occurs.

• Keep out of reach of children.

If swallowed, get medical help or contact a Poison Control Center right away.

Directions

apply to underarms only

Inactive ingredients

Water (Aqua), PPG-11 Stearyl Ether, Steareth-2, Steareth-20, Fragrance (Parfum), Glycerin.

Questions?

Call toll-free 1-800-761-3683

INSTRUCTIONS FOR USE

• Shake well with cap on
• Apply to underarms
• Replace cap